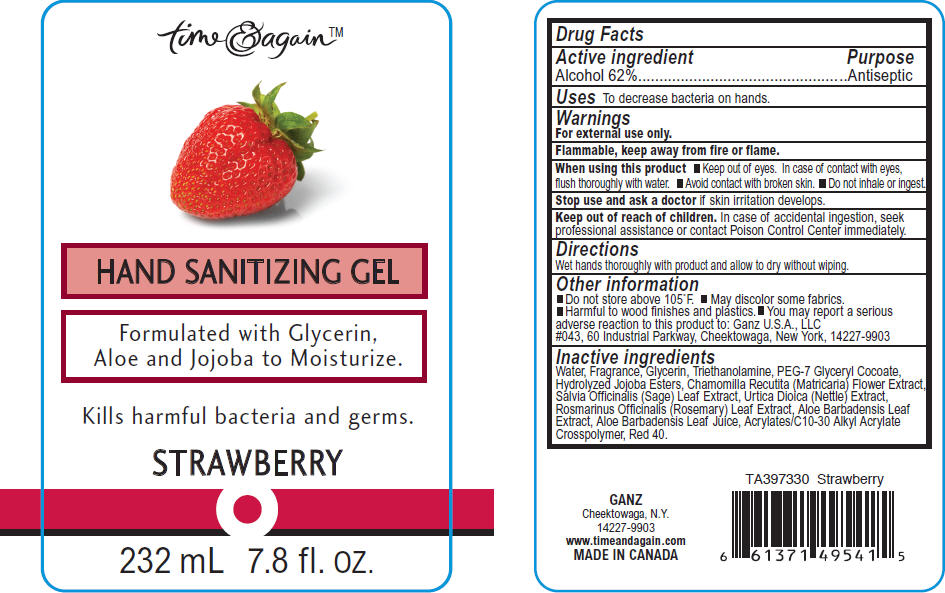 DRUG LABEL: HAND SANITIZING 
NDC: 65365-004 | Form: GEL
Manufacturer: Sigan Industries
Category: otc | Type: HUMAN OTC DRUG LABEL
Date: 20110314

ACTIVE INGREDIENTS: ALCOHOL 62 mL/100 mL
INACTIVE INGREDIENTS: WATER; GLYCERIN; TROLAMINE; CARBOMER COPOLYMER TYPE A; GLYCERYL COCOATE; FD&C RED NO. 40; JOJOBA OIL; CHAMAEMELUM NOBILE FLOWER; SAGE; URTICA DIOICA LEAF; ROSEMARY; ALOE VERA LEAF

time & again™
HAND SANITIZING GEL
STRAWBERRY

Drug Facts

Active ingredient

Alcohol 62%

Purpose

Antiseptic

Uses

To decrease bacteria on hands.

Warnings

For external use only.

Flammable, keep away from fire or flame.

When using this product

- Keep out of eyes. In case of contact with eyes, flush thoroughly with water.
- Avoid contact with broken skin.
- Do not inhale or ingest.

Stop use and ask a doctor if skin irritation develops.

Keep out of reach of children. In case of accidental ingestion, seek professional assistance or contact Poison Control Center immediately.

Directions

Wet hands thoroughly with product and allow to dry without wiping.

Other information

- Do not store above 105°F.
- May discolor some fabrics.
- Harmful to wood finishes and plastics.
- You may report a serious adverse reaction to this product to: Ganz U.S.A., LLC #043, 60 Industrial Parkway, Cheektowaga, New York, 14227-9903

Inactive ingredients

Water, Fragrance, Glycerin, Triethanolamine, PEG-7 Glyceryl Cocoate, Hydrolyzed Jojoba Esters, Chamomilla Recutita (Matricaria) Flower Extract, Salvia Officinalis (Sage) Leaf Extract, Urtica Dioica (Nettle) Extract, Rosmarinus Officinalis (Rosemary) Leaf Extract, Aloe Barbadensis Leaf Extract, Aloe Barbadensis Leaf Juice, Acrylates/C10-30 Alkyl Acrylate Crosspolymer, Red 40.

PRINCIPAL DISPLAY PANEL - 232 mL Bottle Label

time & again™

HAND SANITIZING GEL

Formulated with Glycerin,
Aloe and Jojoba to Moisturize.

Kills harmful bacteria and germs.

STRAWBERRY

232 mL 7.8 fl. OZ.